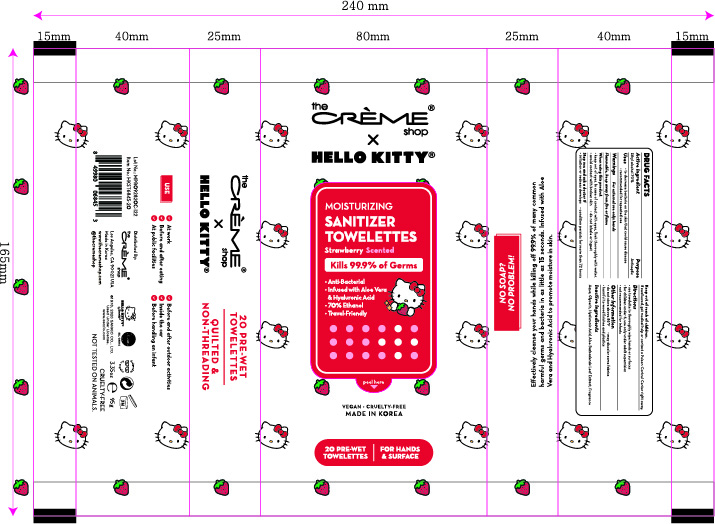 DRUG LABEL: The creme shop Moisturizing Sanitizer Towelettes Strawberry Scented
NDC: 74741-9201 | Form: CLOTH
Manufacturer: MPRBRAIN CO.LTD
Category: otc | Type: HUMAN OTC DRUG LABEL
Date: 20200910

ACTIVE INGREDIENTS: ALCOHOL 0.7 1/1 1
INACTIVE INGREDIENTS: ALOE VERA LEAF; GLYCERIN; HYALURONIC ACID; WATER

The creme shop Moisturizing Sanitizer Towelettes Strawberry Scented : 20 Towelettes
74741-9201-1